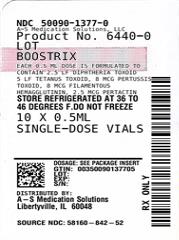 DRUG LABEL: BOOSTRIX
NDC: 50090-1377 | Form: SUSPENSION
Manufacturer: A-S Medication Solutions
Category: other | Type: VACCINE LABEL
Date: 20250331

ACTIVE INGREDIENTS: CLOSTRIDIUM TETANI TOXOID ANTIGEN (FORMALDEHYDE INACTIVATED) 5 [iU]/0.5 mL; CORYNEBACTERIUM DIPHTHERIAE TOXOID ANTIGEN (FORMALDEHYDE INACTIVATED) 2.5 [iU]/0.5 mL; BORDETELLA PERTUSSIS TOXOID ANTIGEN (FORMALDEHYDE, GLUTARALDEHYDE INACTIVATED) 8 ug/0.5 mL; BORDETELLA PERTUSSIS FILAMENTOUS HEMAGGLUTININ ANTIGEN (FORMALDEHYDE INACTIVATED) 8 ug/0.5 mL; BORDETELLA PERTUSSIS PERTACTIN ANTIGEN (FORMALDEHYDE INACTIVATED) 2.5 ug/0.5 mL
INACTIVE INGREDIENTS: ALUMINUM HYDROXIDE; FORMALDEHYDE; SODIUM CHLORIDE; PEG-20 SORBITAN OLEATE

HIGHLIGHTS OF PRESCRIBING INFORMATION

These highlights do not include all the information needed to use BOOSTRIX safely and effectively. See full prescribing information for BOOSTRIX.
BOOSTRIX (Tetanus Toxoid, Reduced Diphtheria Toxoid and Acellular Pertussis Vaccine, Adsorbed) injectable suspension, for intramuscular use
Initial U.S. Approval: 2005

1 INDICATIONS AND USAGE

BOOSTRIX is a vaccine indicated for:

- active booster immunization against tetanus, diphtheria, and pertussis in individuals aged 10 years and older, (1)
- immunization during the third trimester of pregnancy to prevent pertussis in infants younger than 2 months of age. (1)

2 DOSAGE AND ADMINISTRATION

For intramuscular use only.

- Each dose of BOOSTRIX is administered as a 0.5-mL injection. (2.2)
- An initial dose of BOOSTRIX is administered 5 years or more after the last dose of the Diphtheria and Tetanus Toxoids and Acellular Pertussis (DTaP) series or 5 years or more after a dose of Tetanus and Diphtheria Toxoids Adsorbed (Td). BOOSTRIX may be administered as an additional dose 9 years or more after the initial dose of Tetanus Toxoid, Reduced Diphtheria Toxoid and Acellular Pertussis Vaccine Adsorbed (Tdap). (2.2)
- BOOSTRIX may be administered for tetanus prophylaxis for wound management. For management of a tetanus-prone wound, a dose of BOOSTRIX may be administered if at least 5 years have elapsed since previous receipt of a tetanus toxoid-containing vaccine. (2.2)
- To provide protection against pertussis in infants younger than 2 months of age, administer BOOSTRIX during the third trimester of pregnancy. (2.2)

3 DOSAGE FORMS AND STRENGTHS

Single-dose vials and single-dose prefilled syringes containing a 0.5-mL suspension for injection. (3)

4 CONTRAINDICATIONS

- Severe allergic reaction (e.g., anaphylaxis) after a previous dose of any tetanus toxoid-, diphtheria toxoid-, or pertussis antigen-containing vaccine or to any component of BOOSTRIX. (4.1)
- Encephalopathy within 7 days of administration of a previous pertussis antigen-containing vaccine. (4.2)

5 WARNINGS AND PRECAUTIONS

- If Guillain-Barré syndrome occurred within 6 weeks of receipt of a prior vaccine containing tetanus toxoid, the risk of Guillain-Barré syndrome may be increased following a subsequent dose of tetanus toxoid-containing vaccine, including BOOSTRIX. (5.2)
- Progressive or unstable neurologic conditions are reasons to defer vaccination with a pertussis-containing vaccine, including BOOSTRIX. (5.3)
- Persons who experienced an Arthus-type hypersensitivity reaction following a prior dose of a tetanus toxoid-containing vaccine should not receive BOOSTRIX unless at least 10 years have elapsed since the last dose of a tetanus toxoid-containing vaccine. (5.4)

6 ADVERSE REACTIONS

- Common solicited adverse reactions (≥15%) in adolescents (aged 10 to 18 years) were pain, redness, and swelling at the injection site; increase in arm circumference of the injected arm; headache; fatigue; and gastrointestinal symptoms. (6.1)
- Common solicited adverse reactions (≥15%) in adults (aged 19 to 64 years) were pain, redness, and swelling at the injection site; headache; fatigue; and gastrointestinal symptoms. (6.1)
- The most common solicited adverse reaction (≥15%) in the elderly (aged 65 years and older) was pain at the injection site. (6.1)

To report SUSPECTED ADVERSE REACTIONS, contact GlaxoSmithKline at 1-888-825-5249 or VAERS at 1-800-822-7967 or www.vaers.hhs.gov.

FULL PRESCRIBING INFORMATION

1 INDICATIONS AND USAGE

BOOSTRIX is indicated for:

• active booster immunization against tetanus, diphtheria, and pertussis in individuals aged 10 years and older,

• immunization during the third trimester of pregnancy to prevent pertussis in infants younger than 2 months of age.

2 DOSAGE AND ADMINISTRATION

For intramuscular use only.

2.1 Preparation for Administration

Parenteral drug products should be inspected visually for particulate matter and discoloration prior to administration, whenever solution and container permit. Do not use the vaccine if either of these conditions exist. Shake vigorously to obtain a homogeneous, turbid, white suspension before administration. Do not use if resuspension does not occur with vigorous shaking.

For the prefilled syringes, attach a sterile needle and administer intramuscularly.

For the vials, use a sterile needle and sterile syringe to withdraw the 0.5-mL dose and administer intramuscularly. Changing needles between drawing vaccine from a vial and injecting it into a recipient is not necessary unless the needle has been damaged or contaminated.

2.2 Administration, Dose, and Schedule

BOOSTRIX is administered as a 0.5-mL intramuscular injection into the deltoid muscle of the upper arm.

Active Booster Immunization

An initial dose of BOOSTRIX is administered 5 years or more after the last dose of the Diphtheria and Tetanus Toxoids and Acellular Pertussis (DTaP) series or 5 years or more after a dose of Tetanus and Diphtheria Toxoids Adsorbed (Td).

BOOSTRIX may be administered as an additional dose 9 years or more after the initial dose of Tetanus Toxoid, Reduced Diphtheria Toxoid and Acellular Pertussis Vaccine Adsorbed (Tdap).

BOOSTRIX may be administered for tetanus prophylaxis for wound management. For management of a tetanus-prone wound, a dose of BOOSTRIX may be administered if at least 5 years have elapsed since previous receipt of a tetanus toxoid-containing vaccine.

Immunization During the Third Trimester of Pregnancy

To prevent pertussis in infants younger than 2 months of age, administer BOOSTRIX to pregnant individuals during the third trimester of pregnancy.

2.3 Additional Dosing Information

The use of BOOSTRIX as a primary series or to complete the primary series for diphtheria, tetanus, or pertussis has not been established.

3 DOSAGE FORMS AND STRENGTHS

BOOSTRIX is a suspension for injection available in 0.5-mL single-dose vials and prefilled TIP-LOK syringes.

4 CONTRAINDICATIONS

4.1 Severe Allergic Reaction

Do not administer BOOSTRIX to individuals with a known history of severe allergic reaction (e.g., anaphylaxis) to any component of BOOSTRIX or after a previous dose of any tetanus toxoid-, diphtheria toxoid-, or pertussis antigen-containing vaccine [see Description (11)].

4.2 Encephalopathy

Encephalopathy within 7 days of administration of a previous dose of a pertussis antigen-containing vaccine that is not attributable to another identifiable cause is a contraindication to administration of any pertussis antigen-containing vaccine, including BOOSTRIX.

5 WARNINGS AND PRECAUTIONS

5.1 Management of Acute Allergic Reactions

Appropriate medical treatment to manage allergic reactions must be immediately available in the event an acute allergic reaction occurs following administration of BOOSTRIX.

5.2 Guillain-Barré Syndrome and Brachial Neuritis

If Guillain-Barré syndrome occurred within 6 weeks of receipt of a prior vaccine containing tetanus toxoid, the risk of Guillain-Barré syndrome may be increased following a subsequent dose of tetanus toxoid-containing vaccine, including BOOSTRIX. A review by the Institute of Medicine (IOM) found evidence for a causal relationship between receipt of tetanus toxoid and both Guillain-Barré syndrome and brachial neuritis.^1

5.3 Progressive or Unstable Neurologic Disorders

Progressive or unstable neurologic conditions (e.g., cerebrovascular events, acute encephalopathic conditions) are reasons to defer vaccination with a pertussis-containing vaccine, including BOOSTRIX. It is not known whether administration of BOOSTRIX to persons with an unstable or progressive neurologic disorder might hasten manifestations of the disorder or affect the prognosis. Administration of BOOSTRIX to persons with an unstable or progressive neurologic disorder may result in diagnostic confusion between manifestations of the underlying illness and possible adverse effects of vaccination.

5.4 Arthus-Type Hypersensitivity

Persons who experienced an Arthus-type hypersensitivity reaction following a prior dose of a tetanus toxoid-containing vaccine usually have a high serum tetanus antitoxin level and should not receive BOOSTRIX or other tetanus toxoid-containing vaccines unless at least 10 years have elapsed since the last dose of tetanus toxoid-containing vaccine.

5.5 Altered Immunocompetence

As with any vaccine, if administered to immunosuppressed persons, including individuals receiving immunosuppressive therapy, the expected immune response may not be obtained.

5.6 Syncope

Syncope (fainting) may occur in association with administration of injectable vaccines, including BOOSTRIX. Procedures should be in place to avoid injury from fainting.

6 ADVERSE REACTIONS

6.1 Clinical Trials Experience

Because clinical trials are conducted under widely varying conditions, adverse reaction rates observed in the clinical trials of a vaccine cannot be directly compared with rates in the clinical trials of another vaccine and may not reflect the rates observed in practice.

Table 1 provides an overview of the studies that evaluated the safety of BOOSTRIX in various populations.

Table 1. Studies Conducted with BOOSTRIX and the Non-U.S. Formulation of BOOSTRIX
Clinical Studies | Age | Trial Arms (Number of Subjects Vaccinated)
Initial-Dose Studies
U.S. Adolescent Study (NCT00109330) | 10 to 18 Years | BOOSTRIX (3,080); Td (1,034)
German Adolescent Study (NCT00263679) | 10 to 12 Years | BOOSTRIX (319)
U.S. Adult Study (NCT00346073) | 19 to 64 Years | BOOSTRIX (1,522); Tdap (762)
U.S. Elderly Study (NCT00835237) | ≥65 Years | BOOSTRIX (887); Td (445)
Revaccination Studies (all subjects were vaccinated with BOOSTRIX and trial arms were defined based on initial-dose vaccination; subjects in the Control trial arm received a first dose of BOOSTRIX)
U.S. Revaccination Study – 10 Years after Initial Td or BOOSTRIX Dose (NCT01738477) | 20 to 29 Years | BOOSTRIX (128); Td (37)
U.S. Revaccination Study – 9 Years after Initial BOOSTRIX or Tdap Dose (NCT00489970) | 28 to 73 Years | BOOSTRIX (309); Tdap (138); Control (362)
Concomitant Vaccine Studies
Concomitant Vaccination with Meningococcal Conjugate Vaccine (MCV4) (NCT00282295) | 11 to 18 Years | BOOSTRIX+MCV4 (446); BOOSTRIX→MCV4 (446); MCV4→BOOSTRIX (449)
Concomitant Vaccination with Inactivated Trivalent Influenza Vaccine (TIV) (NCT00385255) | 19 to 64 Years | BOOSTRIX+TIV (748); TIV→BOOSTRIX (749)
Concomitant Vaccination with SHINGRIX (Zoster Vaccine Recombinant, Adjuvanted) (NCT02052596) | ≥50 Years | BOOSTRIX+SHINGRIX (412); BOOSTRIX→SHINGRIX (418)
Study in Pregnant Women
Vaccination during the Third Trimester of Pregnancy (NCT02377349) | 18 to 45 Years | Non-U.S. formulation of BOOSTRIX/Tdapa (341) Placebo (346)
a Non-U.S. formulation of BOOSTRIX contains the same antigens and in the same quantities as BOOSTRIX. The non-U.S. formulation is manufactured to contain 0.5 mg aluminum per dose. The U.S. formulation is manufactured to contain 0.3 mg aluminum per dose.

In these studies, subjects were monitored for solicited adverse events using standardized diary cards during the 4 days (Days 0 to 3), 7 days (Days 0 to 6), 8 days (Days 0 to 7), or 15 days (Days 0 to 14) following vaccination. Unsolicited adverse events were monitored for the 30-day period following vaccination (Days 0 to 29) or for the 31-day period following vaccination (Days 0 to 30).

Serious adverse events were monitored for 6 months post-vaccination in the initial-dose studies (NCT00109330, NCT00263679, NCT00346073, NCT00835237), for the 31-day (Days 0 to 30) period post-vaccination in the revaccination (NCT01738477, NCT00489970), and the concomitant-vaccine administration studies with MCV4 and TIV (NCT00282295, NCT00385255), for up to 12 months (Day 0 up to study end) post-vaccination in the concomitant administration study with SHINGRIX (NCT02052596), and from vaccination through 2 months after delivery in the study of pregnant individuals (NCT02377349).

Initial-Dose Studies

In clinical studies, 4,949 adolescents (aged 10 to 18 years) and 4,076 adults (aged 19 years and older) were vaccinated with a single dose of BOOSTRIX. Of these adolescents, 1,341 were vaccinated with BOOSTRIX in a coadministration study with meningococcal conjugate vaccine [see Clinical Studies (14.5)]. Of these adults, 1,104 were aged 65 years and older [see Clinical Studies (14.2)]. A total of 860 adults aged 19 years and older received concomitant vaccination with BOOSTRIX and influenza vaccines in a coadministration study [see Clinical Studies (14.6)].

Solicited Adverse Events in the U.S. Adolescent Study: Table 2 presents the solicited local adverse reactions and general adverse events within 15 days of vaccination with BOOSTRIX or Td vaccine for the total vaccinated cohort.

The primary safety endpoint was the incidence of Grade 3 pain (spontaneously painful and/or prevented normal activity) at the injection site within 15 days of vaccination. Grade 3 pain was reported in 4.6% of those who received BOOSTRIX compared with 4.0% of those who received the Td vaccine. The difference in rate of Grade 3 pain was within the pre-defined clinical limit for non-inferiority (upper limit of the 95% Confidence Interval [CI] for the difference [BOOSTRIX minus Td] ≤4%).

Table 2. Rates of Solicited Local Adverse Reactions or General Adverse Events within the 15-Daya Post-Vaccination Period in Adolescents Aged 10 to 18 Years (Total Vaccinated Cohort)
Adverse Reactions/Adverse Events | BOOSTRIX; (n = 3,032); % | Td; (n = 1,013); %
Local
Pain, anyb | 75 | 72
Pain, Grade 2 or 3b | 51 | 43
Pain, Grade 3c | 5 | 4
Redness, any | 23 | 20
Redness, >20 mm | 4 | 4
Redness, ≥50 mm | 2 | 2
Swelling, any | 21 | 20
Swelling, >20 mm | 5 | 5
Swelling, ≥50 mm | 3 | 3
Arm circumference increase, >5 mmd | 28 | 30
Arm circumference increase, >20 mmd | 2 | 2
Arm circumference increase, >40 mmd | 1 | 0.3
General
Headache, any | 43 | 42
Headache, Grade 2 or 3b | 16 | 13
Headache, Grade 3 | 4 | 3
Fatigue, any | 37 | 37
Fatigue, Grade 2 or 3 | 14 | 13
Fatigue, Grade 3 | 4 | 3
Gastrointestinal symptoms, anye | 26 | 26
Gastrointestinal symptoms, Grade 2 or 3e | 10 | 10
Gastrointestinal symptoms, Grade 3e | 3 | 3
Fever, ≥99.5°F (37.5°C)f | 14 | 13
Fever, >100.4°F (38.0°C)f | 5 | 5
Fever, >102.2°F (39.0°C)f | 1 | 1
Grade 2 = Local: painful when limb moved; General: interfered with normal activity.
Grade 3 = Local: spontaneously painful and/or prevented normal activity; General: prevented normal activity.
a Day of vaccination and the next 14 days.
b Statistically significantly higher (P <0.05) following BOOSTRIX as compared with Td vaccine.
c Grade 3 injection site pain following BOOSTRIX was not inferior to Td vaccine (upper limit of 2-sided 95% CI for the difference [BOOSTRIX minus Td] in the percentage of subjects ≤4%).
d Mid-upper region of the vaccinated arm.
e Gastrointestinal symptoms included nausea, vomiting, diarrhea, and/or abdominal pain.
f Oral temperatures or axillary temperatures.

Unsolicited Adverse Events in the U.S. Adolescent Study: The incidence of unsolicited adverse events reported in the 31 days after vaccination was comparable between the 2 groups (25.4% and 24.5% for BOOSTRIX and Td vaccine, respectively).

Solicited Adverse Events in the German Adolescent Study: BOOSTRIX was administered to 319 children aged 10 to 12 years previously vaccinated with 5 doses of acellular pertussis antigen-containing vaccines; 193 of these subjects received 5 doses of INFANRIX (Diphtheria and Tetanus Toxoids and Acellular Pertussis Vaccine Adsorbed). Table 3 presents the rates of solicited local adverse reactions and fever within 15 days of vaccination for those subjects who had previously been vaccinated with 5 doses of INFANRIX. No cases of whole arm swelling were reported. Two individuals (2/193) reported large injection site swelling (range: 110 to 200 mm diameter), in 1 case associated with Grade 3 pain. Neither individual sought medical attention. These episodes were reported to resolve without sequelae within 5 days.

Table 3. Rates of Solicited Local Adverse Reactions and Fever Reported within the 15-Daya Post-Vaccination Period following Administration of BOOSTRIX in Adolescents Aged 10 to 12 Years Who Had Previously Received 5 Doses of INFANRIX
Adverse Reactions and Fever | BOOSTRIX; (n = 193); %
Pain, any | 62
Pain, Grade 2 or 3 | 33
Pain, Grade 3 | 6
Redness, any | 48
Redness, >20 mm | 15
Redness, ≥50 mm | 11
Swelling, any | 39
Swelling, >20 mm | 18
Swelling, ≥50 mm | 14
Fever, ≥99.5°F (37.5°C)b | 9
Fever, >100.4°F (38.0°C)b | 4
Fever, >102.2°F (39.0°C)b | 1
INFANRIX = Diphtheria and Tetanus Toxoids and Acellular Pertussis Vaccine Adsorbed manufactured by GlaxoSmithKline Biologics.
n = Number of subjects with local/general symptoms sheets completed.
Grade 2 = Painful when limb moved.
Grade 3 = Spontaneously painful and/or prevented normal activity.
a Day of vaccination and the next 14 days.
b Oral temperatures or axillary temperatures.

Solicited Adverse Events in the U.S. Adult (Aged 19 to 64 Years) Study: Table 4 presents solicited local adverse reactions and general adverse events within 15 days of vaccination with BOOSTRIX or the comparator Tdap vaccine for the total vaccinated cohort.

Table 4. Rates of Solicited Local Adverse Reactions or General Adverse Events within the 15-Daya Post-Vaccination Period in Adults Aged 19 to 64 Years (Total Vaccinated Cohort)
Adverse Reactions/Adverse Events | BOOSTRIX; (n = 1,480); % | Tdap; (n = 741); %
Local
Pain, any | 61 | 69
Pain, Grade 2 or 3 | 35 | 44
Pain, Grade 3 | 2 | 2
Redness, any | 21 | 27
Redness, >20 mm | 4 | 6
Redness, ≥50 mm | 2 | 2
Swelling, any | 18 | 26
Swelling, >20 mm | 4 | 6
Swelling, ≥50 mm | 1 | 3
General
Headache, any | 30 | 31
Headache, Grade 2 or 3 | 11 | 11
Headache, Grade 3 | 2 | 2
Fatigue, any | 28 | 29
Fatigue, Grade 2 or 3 | 9 | 9
Fatigue, Grade 3 | 3 | 1
Gastrointestinal symptoms, anyb | 16 | 18
Gastrointestinal symptoms, Grade 2 or 3b | 4 | 6
Gastrointestinal symptoms, Grade 3b | 1 | 1
Fever, ≥99.5°F (37.5°C)c | 6 | 8
Fever, >100.4°F (38.0°C)c | 1 | 2
Fever, >102.2°F (39.0°C)c | 0.1 | 0.4
Tdap = ADACEL (Tetanus Toxoid, Reduced Diphtheria Toxoid and Acellular Pertussis Vaccine Adsorbed, a Tdap vaccine manufactured by Sanofi Pasteur).
n = Number of subjects in the total vaccinated cohort with local/general symptoms sheets completed.
Grade 2 = Local: painful when limb moved; General: interfered with normal activity.
Grade 3 = Local/General: prevented normal activity.
a Day of vaccination and the next 14 days.
b Gastrointestinal symptoms included nausea, vomiting, diarrhea, and/or abdominal pain.
c Oral temperatures.

Unsolicited Adverse Events in the U.S. Adult (Aged 19 to 64 Years) Study: The incidence of unsolicited adverse events reported in the 31 days after vaccination was comparable between the 2 groups (17.8% and 22.2% for BOOSTRIX and Tdap vaccine, respectively).

Solicited Adverse Events in the U.S. Elderly (Aged 65 Years and Older) Study: Table 5 presents solicited local adverse reactions and general adverse events within 4 days of vaccination with BOOSTRIX or the comparator Td vaccine for the total vaccinated cohort.

Table 5. Rates of Solicited Local Adverse Reactions or General Adverse Events within 4 Daysa of Vaccination in the Elderly Aged 65 Years and Older (Total Vaccinated Cohort)
Adverse Reactions/Adverse Events | BOOSTRIX; % | Td; %
Local | (n = 882) | (n = 444)
Pain, any | 22 | 28
Pain, Grade 2 or 3 | 8 | 10
Pain, Grade 3 | 0.2 | 1
Redness, any | 11 | 13
Redness, >20 mm | 1 | 3
Redness, ≥50 mm | 1 | 1
Swelling, any | 8 | 12
Swelling, >20 mm | 2 | 3
Swelling, ≥50 mm | 1 | 1
General | (n = 882) | (n = 445)
Fatigue, any | 13 | 15
Fatigue, Grade 2 or 3 | 3 | 3
Fatigue, Grade 3 | 1 | 1
Headache, any | 12 | 12
Headache, Grade 2 or 3 | 2 | 2
Headache, Grade 3 | 1 | 0
Gastrointestinal symptoms, anyb | 8 | 9
Gastrointestinal symptoms, Grade 2 or 3b | 2 | 2
Gastrointestinal symptoms, Grade 3b | 0.3 | 0.4
Fever, ≥99.5°F (37.5°C)c | 2 | 3
Fever, >100.4°F (38.0°C)c | 0.2 | 0.2
Fever, >102.2°F (39.0°C)c | 0 | 0
Td = DECAVAC (Tetanus and Diphtheria Toxoids Adsorbed, a U.S.-licensed Td vaccine, manufactured by Sanofi Pasteur).
n = Number of subjects with a documented dose.
Grade 2 = Local: painful when limb moved; General: interfered with normal activity.
Grade 3 = Local/General: prevented normal activity.
a Day of vaccination and the next 3 days.
b Gastrointestinal symptoms included nausea, vomiting, diarrhea, and/or abdominal pain.
c Oral temperatures.

Unsolicited Adverse Events in the U.S. Elderly (Aged 65 Years and Older) Study: The incidence of unsolicited adverse events reported in the 31 days after vaccination was comparable between the 2 groups (17.1% and 14.4% for BOOSTRIX and Td vaccine, respectively).

Serious Adverse Events (SAEs): In the U.S. and German adolescent safety studies, no serious adverse events were reported to occur within 31 days of vaccination. During the 6-month extended safety evaluation period, no serious adverse events that were of potential autoimmune origin or new onset and chronic in nature were reported to occur. In non-U.S. adolescent studies in which serious adverse events were monitored for up to 37 days, 1 subject was diagnosed with insulin-dependent diabetes 20 days following administration of BOOSTRIX. No other serious adverse events of potential autoimmune origin or that were new onset and chronic in nature were reported to occur in these studies. In the U.S. adult (aged 19 to 64 years) study, serious adverse events were reported to occur during the entire study period (0-6 months) by 1.4% and 1.7% of subjects who received BOOSTRIX and the comparator Tdap vaccine, respectively. During the 6-month extended safety evaluation period, no serious adverse events of a neuroinflammatory nature or with information suggesting an autoimmune etiology were reported in subjects who received BOOSTRIX. In the U.S. elderly (aged 65 years and older) study, serious adverse events were reported to occur by 0.7% and 0.9% of subjects who received BOOSTRIX and the comparator Td vaccine, respectively, during the 31-day period after vaccination. Serious adverse events were reported to occur by 4.2% and 2.2% of subjects who received BOOSTRIX and the comparator Td vaccine, respectively, during the 6-month period after vaccination.

Revaccination Studies

U.S. Revaccination Studies in Adults: In 2 clinical studies, 974 adults (aged 20 years and older) were vaccinated with a dose of BOOSTRIX [see Clinical Studies (14.4)].

Solicited Adverse Events in the U.S. Revaccination Studies: Table 6 presents solicited local adverse reactions and general adverse events within 4 days of vaccination with BOOSTRIX for the total vaccinated cohort in both studies.

Table 6. Rates of Solicited Local Adverse Reactions or General Adverse Events within 4 Daysa of Vaccination in Adults Aged 20 to 73 Years (Total Vaccinated Cohort)
Adverse Reactions/ Adverse Events | Adults Aged 20 to 29 Years |  | Adults Aged 28 to 73 Years
Adverse Reactions/ Adverse Events | BOOSTRIXb; (n = 125); % | Tdc; (n = 36); % | BOOSTRIXd; (n = 306); % | Tdape; (n = 137); % | Controlf; (n = 358); %
Local
Pain, any | 78 | 58 | 59 | 61 | 37
Pain, Grade 2 or 3 | 33 | 19 | 17 | 15 | 9
Pain, Grade 3 | 5 | 6 | 1 | 1 | 1
Redness, any | 38 | 42 | 24 | 23 | 15
Redness, >20 mm | 4 | 0 | 6 | 4 | 1
Redness, ≥50 mmg | 1 | 0 | 2 | 2 | 0
Swelling, any | 24 | 19 | 19 | 19 | 12
Swelling, >20 mm | 2 | 3 | 3 | 3 | 3
Swelling, ≥50 mmh | 0 | 0 | 1 | 2 | 1
General
Headache, any | 32 | 22 | 17 | 18 | 15
Headache, Grade 2 or 3 | 10 | 3 | 4 | 4 | 2
Headache, Grade 3 | 2 | 0 | 0 | 1 | 0.3
Fatigue, any | 30 | 22 | 23 | 17 | 14
Fatigue, Grade 2 or 3 | 14 | 3 | 8 | 7 | 3
Fatigue, Grade 3 | 2 | 0 | 1 | 1 | 0
Gastrointestinal symptoms, anyi | 9 | 3 | 9 | 3 | 8
Gastrointestinal symptoms, Grade 2 or 3i | 2 | 0 | 2 | 0 | 3
Gastrointestinal symptoms, Grade 3i | 2 | 0 | 0 | 0 | 0
Fever, ≥100.4°F (38.0°C)j | 1 | 0 | 1 | 0 | 1
Fever, >102.2°F (39.0°C)j | 0 | 0 | 0.3 | 0 | 0
Td = Tetanus and Diphtheria Toxoids Adsorbed for Adult Use manufactured by MassBiologics.
Tdap = ADACEL (Tetanus Toxoid, Reduced Diphtheria Toxoid and Acellular Pertussis Vaccine Adsorbed, a Tdap vaccine manufactured by Sanofi Pasteur).
n = Number of subjects with a documented dose.
Grade 2 = Local: painful when limb moved and interfered with normal activities; General: interfered with normal activity.
Grade 3 = Local: significant pain at rest and/or prevented normal activity; General: prevented normal activity.
a Day of vaccination and the next 3 days.
b Subjects who were revaccinated with BOOSTRIX 10 years after initial vaccination with BOOSTRIX.
c Subjects who received a dose of BOOSTRIX 10 years after initial vaccination with Td vaccine.
d Subjects who were revaccinated with BOOSTRIX 9 years after initial vaccination with BOOSTRIX.
e Subjects who received a dose of BOOSTRIX 9 years after initial vaccination with Tdap vaccine.
f Control Group = Newly enrolled subjects who received an initial dose of BOOSTRIX.
g In the study of adults aged 20 to 29 years, redness >50 mm was recorded.
h In the study of adults aged 20 to 29 years, swelling >50 mm was recorded.
i Gastrointestinal symptoms included nausea, vomiting, diarrhea, and/or abdominal pain.
j Oral temperatures.

Concomitant Vaccination with Meningococcal Conjugate Vaccine in Adolescents

Table 7 presents the percentages of subjects experiencing local reactions at the injection site for BOOSTRIX and solicited general events following BOOSTRIX. The incidence of unsolicited adverse events reported in the 31 days after any vaccination was similar following each dose of BOOSTRIX in all cohorts.

Table 7. Rates of Solicited Local Adverse Reactions or General Adverse Events Reported within the 4-Day Post-Vaccination Period following Administration of BOOSTRIX in Individuals Aged 11 to 18 Years (Total Vaccinated Cohort)
Adverse Reactions/Adverse Events | BOOSTRIX+MCV4a; (n = 441); % | BOOSTRIX→MCV4b; (n = 432-433); % | MCV4→BOOSTRIXc; (n = 441); %
Local (at injection site for BOOSTRIX)
Pain, any | 70 | 70 | 48
Redness, any | 23 | 26 | 18
Swelling, any | 18 | 18 | 12
General (following administration of BOOSTRIX)
Fatigue | 34 | 32 | 20
Headache | 34 | 31 | 17
Gastrointestinal symptomsd | 15 | 15 | 8
Fever, ≥99.5°F (37.5°C)e | 5 | 4 | 2
MCV4 = MENACTRA (Meningococcal [Groups A, C, Y, and W-135] Polysaccharide Diphtheria Toxoid Conjugate Vaccine), Sanofi Pasteur.
n = Number of subjects in the total vaccinated cohort with local/general symptoms sheets completed.
a BOOSTRIX+MCV4 = Concomitant vaccination with BOOSTRIX and MENACTRA.
b BOOSTRIX→MCV4 = BOOSTRIX followed by MCV4 1 month later.
c MCV4→BOOSTRIX = MCV4 followed by BOOSTRIX 1 month later.
d Gastrointestinal symptoms included nausea, vomiting, diarrhea, and/or abdominal pain.
e Oral temperatures.

Concomitant Vaccination with SHINGRIX (Zoster Vaccine Recombinant, Adjuvanted) in Adults ≥50 Years

Table 8 presents the percentage of subjects experiencing local reactions at the injection site for BOOSTRIX and SHINGRIX, respectively, and solicited general events following BOOSTRIX and SHINGRIX vaccination when administered concomitantly or separately. The incidence of unsolicited adverse events within the 30-day post‑vaccination period was similar in the concomitant administration and the separate administration control groups.

Table 8. Rates of Solicited Local Adverse Reactions and General Adverse Events Reported within 7 Days Post-Vaccination Period by Study Vaccine in Individuals Aged ≥ 50 Years (Total Vaccinated Cohort)
Adverse Reactions/Adverse Events | Concomitant Administration Groupa; (n = 406-407); % | Separate Administration Control Groupb
Adverse Reactions/Adverse Events | Concomitant Administration Groupa; (n = 406-407); % | BOOSTRIX; (n = 409); % | SHINGRIX; (n = 403, first dose); %
Local/ injection site
Pain, any
BOOSTRIX | 45 | 38 | -
SHINGRIX | 71 | - | 74
Redness, any
BOOSTRIX | 8 | 4 | -
SHINGRIX | 27 | - | 25
Swelling, any
BOOSTRIX | 6 | 5 | -
SHINGRIX | 17 | - | 17
General
Myalgia, any | 44 | 25 | 39
Fatigue, any | 32 | 16 | 27
Headache, any | 26 | 15 | 20
Gastrointestinal symptomsc, any | 13 | 9 | 11
Fever, ≥ 99.5 ° F; (37.5°C)d | 9 | 2 | 6
Shivering, any | 16 | 4 | 9
a Concomitant Administration Group = Dose 1: BOOSTRIX + SHINGRIX, Dose 2: SHINGRIX
b Separate Administration Control Group = Dose 1: BOOSTRIX, Dose 2: SHINGRIX
n = number of subjects with at least one documented dose
% = percentage of subjects reporting the symptom at least once
c Gastrointestinal symptoms included nausea, vomiting, diarrhea, and/or abdominal pain
d Fever was defined as temperature ≥ 37.5°C for oral, axillary or tympanic route

Vaccination During Pregnancy

Safety of non-U.S. formulation BOOSTRIX (0.5 mg aluminum/per dose) during the third trimester of pregnancy was evaluated in study NCT02377349. The safety data with the non-U.S. formulation are relevant because the non-U.S. formulation of BOOSTRIX contains the same antigens and in the same quantities as BOOSTRIX. However, the non-U.S. formulation contains more aluminum per dose (see Table 1).

In the randomized, controlled study NCT02377349, 687 pregnant individuals received the non-U.S. formulation of BOOSTRIX or placebo during the third trimester (341 non-U.S. formulation of BOOSTRIX, 346 placebo [saline]). The placebo recipients received the non-U.S. formulation of BOOSTRIX postpartum. The rates of reported solicited adverse reactions following receipt of the non-U.S. formulation of BOOSTRIX administered during pregnancy were consistent with the rates following receipt of the non-U.S. formulation of BOOSTRIX administered to study participants postpartum. For further information about pregnancy outcomes [see Use in Specific Populations (8.1)].

6.2 Postmarketing Experience

In addition to reports in clinical trials for BOOSTRIX, the following adverse events have been identified in persons aged 10 years and older during postapproval use of BOOSTRIX worldwide. Because these events are reported voluntarily from a population of uncertain size, it is not always possible to reliably estimate their frequency or establish a causal relationship to the vaccine.

Blood and Lymphatic System Disorders

Lymphadenitis, lymphadenopathy.

Immune System Disorders

Allergic reactions, including anaphylactic and anaphylactoid reactions.

Cardiac Disorders

Myocarditis.

General Disorders and Administration Site Conditions

Extensive swelling of the injected limb, injection site induration, injection site inflammation, injection site mass, injection site pruritus, injection site nodule, injection site warmth, injection site reaction.

Musculoskeletal and Connective Tissue Disorders

Arthralgia, back pain, myalgia.

Nervous System Disorders

Convulsions (with and without fever), encephalitis, facial palsy, loss of consciousness, paresthesia, syncope.

Skin and Subcutaneous Tissue Disorders

Angioedema, exanthem, Henoch-Schönlein purpura, rash, urticaria.

7 DRUG INTERACTIONS

7.1 Immunosuppressive Therapies

Immunosuppressive therapies, including irradiation, antimetabolites, alkylating agents, cytotoxic drugs, and corticosteroids (used in greater than physiologic doses), may reduce the immune response to BOOSTRIX.

8 USE IN SPECIFIC POPULATIONS

8.1 Pregnancy

Pregnancy Exposure Registry

There is a pregnancy exposure registry that monitors pregnancy outcomes in women exposed to BOOSTRIX during pregnancy. Healthcare providers are encouraged to register women by calling 1-888-452-9622 or visiting http://pregnancyregistry.gsk.com/boostrix.html.

Risk Summary

All pregnancies have a risk of birth defect, loss, or other adverse outcomes. In the U.S. general population, the estimated background risk of major birth defects and miscarriage in clinically recognized pregnancies is 2% to 4% and 15% to 20%, respectively.

In a randomized, controlled clinical study (NCT02377349), in which the non-U.S. formulation of BOOSTRIX was administered during the third trimester of pregnancy, there were no identified vaccine-related adverse effects on pregnancy or on the fetus/newborn child (see Data).

Available data from the pregnancy registry and from spontaneous and postmarketing reports suggest that the rates of major birth defects and miscarriage in women who received BOOSTRIX within 28 days prior to conception or during pregnancy are consistent with estimated background rates (see Data).

A developmental toxicity study was performed in female rats administered INFANRIX prior to mating and BOOSTRIX during gestation, 0.1 mL at each occasion (a single human dose is 0.5 mL). In a second study, female rats were administered 0.2 mL of BOOSTRIX prior to mating and during the gestation and lactation period. In a third study, female New Zealand White rabbits were given 0.5 mL (full human dose) of BOOSTRIX (non-U.S. formulation) prior to mating and during gestation. These studies revealed no evidence of harm to the fetus due to BOOSTRIX (see Data).

Data

Human Data: Safety data from a randomized (1:1), controlled clinical study (NCT02377349) (341 non-U.S. formulation of BOOSTRIX, 346 placebo pregnancy outcomes) in which the non-U.S. formulation of BOOSTRIX was administered to pregnant women during the third trimester did not reveal any vaccine-related adverse effects on pregnancy or on the fetus/newborn child. Safety data from prospective clinical studies on the use of BOOSTRIX during the first and second trimester of pregnancy are not available.

An assessment of data from the U.S. pregnancy exposure registry over approximately 17 years (2005-2022) included 1,523 prospective reports of exposure to BOOSTRIX within 28 days prior to conception or during pregnancy. Among the 256 reports with known pregnancy outcomes, 19 women were exposed to BOOSTRIX in the first trimester with no major birth defects reported and 3 spontaneous abortions with no apparent birth defect; 28 women were exposed to BOOSTRIX in the second trimester, and 199 women were exposed to BOOSTRIX in the third trimester with no major birth defects reported; 10 women were exposed to BOOSTRIX at an unknown timing in pregnancy with no major birth defects reported.

An assessment of U.S. spontaneous reports and postmarketing data included 810 prospective reports of exposure to BOOSTRIX during pregnancy since May 2005 through 31 August 2022. Among the 138 reports with known pregnancy outcomes, 17 women were exposed to BOOSTRIX in the first trimester with no major birth defects reported and 2 spontaneous abortions with no apparent birth defect; 26 women were exposed to BOOSTRIX in the second trimester, and 92 women were exposed to BOOSTRIX in the third trimester with no major birth defects reported; 3 women were exposed to BOOSTRIX at an unknown timing in pregnancy with no major birth defects reported.

Animal Data: Developmental toxicity studies were performed in female rats and New Zealand White rabbits. In one study, female rats were administered 0.1 mL of INFANRIX (a single human dose is 0.5 mL) by intramuscular injection 30 days prior to mating and 0.1 mL of BOOSTRIX (a single human dose is 0.5 mL) by intramuscular injection on Gestation Days 6, 8, 11, and 15. The antigens in INFANRIX are the same as those in BOOSTRIX, but INFANRIX is formulated with higher quantities of these antigens. In a second study, female rats were administered 0.2 mL of BOOSTRIX by intramuscular injection 28 days and 14 days prior to mating, on Gestation Days 3, 8, 11, and 15, and on Lactation Day 7. In these studies, no adverse effects on embryo-fetal or pre-weaning development up to Postnatal Day 25 were observed; there were no fetal malformations or variations observed. In a third study, female New Zealand White rabbits were administered 0.5 mL (full human dose) of BOOSTRIX (non-U.S. formulation) by intramuscular injection on Premating Days -28 and -14 and on Gestation Days 3, 8, 11, 15, and 24. In this study, no adverse effects on embryo-fetal development related to BOOSTRIX were observed; postnatal development was not evaluated.

8.2 Lactation

Risk Summary

It is not known whether the vaccine components of BOOSTRIX are excreted in human milk. Data are not available to assess the effect of administration of BOOSTRIX on breastfed infants or on milk production/excretion. The developmental and health benefits of breastfeeding should be considered along with the mother’s clinical need for BOOSTRIX and any potential adverse effects on the breastfed child from BOOSTRIX or from the underlying maternal condition. For preventive vaccines, the underlying maternal condition is susceptibility to disease prevented by the vaccine.

8.4 Pediatric Use

BOOSTRIX is not indicated for use in children aged younger than 10 years. Safety and effectiveness of BOOSTRIX in this age group have not been established.

8.5 Geriatric Use

In the initial-dose clinical trials, 1,104 subjects aged 65 years and older received BOOSTRIX; of these subjects, 299 were aged 75 years and older. Adverse events following BOOSTRIX were similar in frequency to those reported with the comparator Td vaccine [see Adverse Reactions (6.1)].

A revaccination study of BOOSTRIX in adults aged 28 to 73 years [see Clinical Studies (14.4)] did not include sufficient numbers of subjects aged 65 and older to determine whether they respond differently from younger subjects.

11 DESCRIPTION

BOOSTRIX (Tetanus Toxoid, Reduced Diphtheria Toxoid and Acellular Pertussis Vaccine, Adsorbed) is a noninfectious, sterile, vaccine for intramuscular administration. It contains tetanus toxoid, diphtheria toxoid, and pertussis antigens (inactivated pertussis toxin [PT] and formaldehyde-treated FHA and PRN). The antigens are the same as those in INFANRIX, but BOOSTRIX is formulated with reduced quantities of these antigens.

Tetanus toxin is produced by growing Clostridium tetani (C. tetani) in a modified Latham medium derived from bovine casein. The diphtheria toxin is produced by growing Corynebacterium diphtheriae (C. diphtheriae) in Fenton medium containing a bovine extract. The bovine materials used in these extracts are sourced from countries which the United States Department of Agriculture (USDA) has determined neither have nor are at risk of bovine spongiform encephalopathy (BSE). Both toxins are detoxified with formaldehyde, concentrated by ultrafiltration, and purified by precipitation, dialysis, and sterile filtration.

The acellular pertussis antigens (PT, FHA, and PRN) are isolated from Bordetella pertussis (B. pertussis) culture grown in modified Stainer-Scholte liquid medium. PT and FHA are isolated from the fermentation broth; PRN is extracted from the cells by heat treatment and flocculation. The antigens are purified in successive chromatographic and precipitation steps. PT is detoxified using glutaraldehyde and formaldehyde. FHA and PRN are treated with formaldehyde.

Each antigen is individually adsorbed onto aluminum hydroxide. Each 0.5-mL dose is formulated to contain 5 Lf of tetanus toxoid, 2.5 Lf of diphtheria toxoid, 8 mcg of inactivated PT, 8 mcg of FHA, and 2.5 mcg of PRN (69 kiloDalton outer membrane protein).

Tetanus and diphtheria toxoid potency is determined by measuring the amount of neutralizing antitoxin in previously immunized guinea pigs. The potency of the acellular pertussis components (inactivated PT and formaldehyde-treated FHA and PRN) is determined by enzyme-linked immunosorbent assay (ELISA) on sera from previously immunized mice.

Each 0.5-mL dose contains aluminum hydroxide as adjuvant (formulated to contain 0.3 mg aluminum) and 4.4 mg of sodium chloride. The aluminum content is measured by assay. Each dose also contains ≤100 mcg of residual formaldehyde and ≤100 mcg of polysorbate 80 (Tween 80).

BOOSTRIX is available in vials and prefilled syringes. The tip cap and rubber plunger stopper of the prefilled syringe are not made with natural rubber latex. The vial stoppers are not made with natural rubber latex.

BOOSTRIX is formulated without preservatives.

12 CLINICAL PHARMACOLOGY

12.1 Mechanism of Action

Active Immunization

Tetanus is a condition manifested primarily by neuromuscular dysfunction caused by a potent exotoxin released by C. tetani. Protection against disease is due to the development of neutralizing antibodies to the tetanus toxin. A serum tetanus antitoxin level of at least 0.01 IU/mL, measured by neutralization assays, is considered the minimum protective level.^2 A level ≥0.1 IU/mL by ELISA has been considered as protective.

Diphtheria is an acute toxin-mediated infectious disease caused by toxigenic strains of C. diphtheriae. Protection against disease is due to the development of neutralizing antibodies to the diphtheria toxin. A serum diphtheria antitoxin level of 0.01 IU/mL, measured by neutralization assays, is the lowest level giving some degree of protection; a level of 0.1 IU/mL by ELISA is regarded as protective. Diphtheria antitoxin levels ≥1.0 IU/mL by ELISA have been associated with long-term protection.^3

Pertussis (whooping cough) is a disease of the respiratory tract caused by B. pertussis. The role of the different components produced by B. pertussis in either the pathogenesis of, or the immunity to, pertussis is not well understood.

Passive Immunization to Prevent Pertussis in Infants

Antibodies to pertussis antigens from individuals vaccinated during the third trimester of pregnancy are transferred transplacentally to prevent pertussis in infants younger than 2 months of age.

13 NONCLINICAL TOXICOLOGY

13.1 Carcinogenesis, Mutagenesis, Impairment of Fertility

BOOSTRIX has not been evaluated for carcinogenic or mutagenic potential, or for impairment of male fertility in animals. Vaccination of female rabbits and rats with BOOSTRIX had no effect on fertility. [See Use in Specific Populations (8.1).]

14 CLINICAL STUDIES

14.1 Effectiveness of BOOSTRIX, INFANRIX, and PEDIARIX

Effectiveness of BOOSTRIX

The effectiveness of the tetanus and diphtheria toxoid components of BOOSTRIX is based on the immunogenicity of the individual antigens compared with U.S.-licensed vaccines using established serologic correlates of protection. The effectiveness of the pertussis components of BOOSTRIX was evaluated by comparison of the immune response of adolescents and adults following an initial dose of BOOSTRIX to the immune response of infants following a 3-dose primary series of INFANRIX or by comparison of the immune response of adults following an additional dose of BOOSTRIX to the immune response of infants following a 3-dose primary series of PEDIARIX. In addition, the ability of BOOSTRIX to induce a booster response to each of the antigens was evaluated.

Efficacy of INFANRIX against Pertussis

The efficacy of a 3-dose primary series of INFANRIX in infants has been assessed in 2 clinical studies: A prospective efficacy trial conducted in Germany employing a household contact study design and a double-blind, randomized, active Diphtheria and Tetanus Toxoids (DT)-controlled trial conducted in Italy sponsored by the National Institutes of Health (NIH) (for details see INFANRIX prescribing information). In the household contact study, the protective efficacy of INFANRIX in infants against WHO-defined pertussis (21 days or more of paroxysmal cough with infection confirmed by culture and/or serologic testing) was calculated to be 89% (95% CI: 77%, 95%). When the definition of pertussis was expanded to include clinically milder disease, with infection confirmed by culture and/or serologic testing, the efficacy of INFANRIX against ≥7 days of any cough was 67% (95% CI: 52%, 78%) and against ≥7 days of paroxysmal cough was 81% (95% CI: 68%, 89%) (for details see INFANRIX prescribing information).

Immune Responses to Pertussis Antigens of PEDIARIX Compared with INFANRIX

The diphtheria, tetanus, and pertussis components in PEDIARIX are the same as those in INFANRIX. The effectiveness of the pertussis component of PEDIARIX was determined in clinical trials by comparison to antibody responses to INFANRIX (for details see PEDIARIX prescribing information).

Immune Responses to Pertussis Antigens of BOOSTRIX Compared with INFANRIX or PEDIARIX

Although a serologic correlate of protection for pertussis has not been established, serological data from a subset of infants immunized with a 3-dose primary series of INFANRIX in the German household contact study were compared with the sera of adolescents and adults immunized with an initial dose of BOOSTRIX [see Clinical Studies (14.2)]. Serological data from infants immunized with a 3-dose primary series of PEDIARIX in an additional pediatric study were compared with the sera of adults immunized with an additional dose of BOOSTRIX [see Clinical Studies (14.4)]. The GMCs to each of the pertussis antigens 1 month following a dose of BOOSTRIX were compared with the GMCs of infants following INFANRIX administered at 3, 4, and 5 months of age or were compared with the GMCs of infants following PEDIARIX administered at 2, 4, and 6 months of age. The majority of subjects in the study of INFANRIX had only anti-PT serology data.

14.2 Immunological Evaluation following an Initial Dose of BOOSTRIX

Adolescents (Aged 10 to 18 years)

In a multicenter, randomized, observer-blinded, controlled study conducted in the United States (NCT00109330), the immune responses to each of the antigens contained in BOOSTRIX were evaluated in sera obtained approximately 1 month after administration of a single dose of vaccine to adolescent subjects (aged 10 to 18 years). Of the subjects enrolled in this study, approximately 76% were aged 10 to 14 years and 24% were aged 15 to 18 years. Approximately 98% of participants in this study had received the recommended series of 4 or 5 doses of either DTwP or a combination of DTwP and DTaP in childhood. The racial/ethnic demographics were as follows: White 85.8%, Black 5.7%, Hispanic 5.6%, Oriental 0.8%, and other 2.1%.

Response to Tetanus and Diphtheria Toxoids: The antibody responses to the tetanus and diphtheria toxoids of BOOSTRIX compared with Td vaccine are shown in Table 9. One month after a single dose, anti-tetanus and anti-diphtheria seroprotective rates (≥0.1 IU/mL by ELISA) and booster response rates were comparable between BOOSTRIX and the comparator Td vaccine.

Table 9. Antibody Responses to Tetanus and Diphtheria Toxoids following BOOSTRIX Compared with Td Vaccine in Adolescents Aged 10 to 18 Years (ATP Cohort for Immunogenicity)
Antibodies | n | % ≥0.1 IU/mLa; (95% CI) | % ≥1.0 IU/mLa; (95% CI) | % Booster Responseb; (95% CI)
Anti-tetanus
BOOSTRIX | 2,469-2,516
Pre-vaccination |  | 97.7 (97.1, 98.3) | 36.8 (34.9, 38.7) | –
Post-vaccination |  | 100 (99.8, 100)c | 99.5 (99.1, 99.7)d | 89.7 (88.4, 90.8)c
Td | 817-834
Pre-vaccination |  | 96.8 (95.4, 97.9) | 39.9 (36.5, 43.4) | –
Post-vaccination |  | 100 (99.6, 100) | 99.8 (99.1, 100) | 92.5 (90.5, 94.2)
Anti-diphtheria
BOOSTRIX | 2,463-2,515
Pre-vaccination |  | 85.8 (84.3, 87.1) | 17.1 (15.6, 18.6) | –
Post-vaccination |  | 99.9 (99.7, 100)c | 97.3 (96.6, 97.9)d | 90.6 (89.4, 91.7)c
Td | 814-834
Pre-vaccination |  | 84.8 (82.1, 87.2) | 19.5 (16.9, 22.4) | –
Post-vaccination |  | 99.9 (99.3, 100) | 99.3 (98.4, 99.7) | 95.9 (94.4, 97.2)
Td = Tetanus and Diphtheria Toxoids, Adsorbed manufactured by MassBiologics.
ATP = According-to-protocol; CI = Confidence Interval.
a Measured by ELISA.
b Booster response: In subjects with pre-vaccination <0.1 IU/mL, post-vaccination concentration ≥0.4 IU/mL. In subjects with pre-vaccination concentration ≥0.1 IU/mL, an increase of at least 4 times the pre-vaccination concentration.
c Seroprotection rate or booster response rate to BOOSTRIX was non-inferior to Td (upper limit of 2-sided 95% CI on the difference for Td minus BOOSTRIX ≤10%).
d Non-inferiority criteria not prospectively defined for this endpoint.

Response to Pertussis Antigens: The booster response rates of adolescents to the pertussis antigens are shown in Table 10. For each of the pertussis antigens the lower limit of the 2-sided 95% CI for the percentage of subjects with a booster response exceeded the pre-defined lower limit of 80% for demonstration of an acceptable booster response.

Table 10. Booster Responses to the Pertussis Antigens following BOOSTRIX in Adolescents Aged 10 to 18 Years (ATP Cohort for Immunogenicity)
Pertussis Antibodies | n | BOOSTRIX; % Booster Responsea (95% CI)
Anti-PT | 2,677 | 84.5 (83.0, 85.9)
Anti-FHA | 2,744 | 95.1 (94.2, 95.9)
Anti-PRN | 2,752 | 95.4 (94.5, 96.1)
ATP = According-to-protocol; CI = Confidence Interval; PT = Pertussis toxin; FHA = Filamentous hemagglutinin; PRN = Pertactin.
a Booster response: In initially seronegative subjects (<5 EL.U./mL), post-vaccination antibody concentrations ≥20 EL.U./mL. In initially seropositive subjects with pre-vaccination antibody concentrations ≥5 EL.U./mL and <20 EL.U./mL, an increase of at least 4 times the pre-vaccination antibody concentration. In initially seropositive subjects with pre-vaccination antibody concentrations ≥20 EL.U./mL, an increase of at least 2 times the pre-vaccination antibody concentration.

The GMCs to each of the pertussis antigens 1 month following a single dose of BOOSTRIX were compared with the GMCs of a subset of infants following a 3-dose primary series of INFANRIX in the German household contact study [see Clinical Studies (14.1)]. Table 11 presents the results for the total immunogenicity cohort in both studies (vaccinated subjects with serology data available for at least 1 pertussis antigen). Anti-PT, anti-FHA, and anti-PRN antibody concentrations observed in adolescents 1 month after a single dose of BOOSTRIX were non-inferior to those infants following a primary vaccination series with INFANRIX.

Table 11. Ratio of GMCs to Pertussis Antigens following 1 Dose of BOOSTRIX in Adolescents Aged 10 to 18 Years Compared with 3 Doses of INFANRIX in Infants (Total Immunogenicity Cohort)
Pertussis Antibodies | BOOSTRIX; (n) | INFANRIX; (n) | GMC Ratio: BOOSTRIX/INFANRIX; (95% CI)
Anti-PT | 2,941 | 2,884 | 1.90 (1.82, 1.99)a
Anti-FHA | 2,979 | 685 | 7.35 (6.85, 7.89)a
Anti-PRN | 2,978 | 631 | 4.19 (3.73, 4.71)a
GMC = Geometric mean antibody concentration, measured in ELISA units; CI = Confidence Interval; PT = Pertussis toxin; FHA = Filamentous hemagglutinin; PRN = Pertactin.
n = Number of subjects for GMC evaluation.
a GMC following BOOSTRIX was non-inferior to GMC following INFANRIX (lower limit of 95% CI for the GMC ratio of BOOSTRIX/INFANRIX >0.67).

Adults (Aged 19 to 64 Years)

A multicenter, randomized, observer-blinded study, conducted in the United States (NCT00346073), evaluated the immunogenicity of BOOSTRIX compared with the licensed comparator Tdap vaccine (Sanofi Pasteur). Vaccines were administered as a single dose to subjects (N = 2,284) who had not received a tetanus-diphtheria booster within 5 years. The immune responses to each of the antigens contained in BOOSTRIX were evaluated in sera obtained approximately 1 month after administration. Approximately 33% of subjects were aged 19 to 29 years, 33% were aged 30 to 49 years, and 34% were aged 50 to 64 years. Among subjects in the combined vaccine groups, 62% were female; 84% of subjects were White, 8% Black, 1% Asian, and 7% were of other racial/ethnic groups.

Response to Tetanus and Diphtheria Toxoids: The antibody responses to the tetanus and diphtheria toxoids of BOOSTRIX compared with the comparator Tdap vaccine are shown in Table 12. One month after a single dose, anti-tetanus and anti-diphtheria seroprotective rates (≥0.1 IU/mL by ELISA) were comparable between BOOSTRIX and the comparator Tdap vaccine.

Table 12. Antibody Responses to Tetanus and Diphtheria Toxoids following 1 Dose of BOOSTRIX Compared with the Comparator Tdap Vaccine in Adults Aged 19 to 64 Years (ATP Cohort for Immunogenicity)
Antibodies |  | % ≥0.1 IU/mLa | % ≥1.0 IU/mLa
Antibodies | n | (95% CI) | (95% CI)
Anti-tetanus
BOOSTRIX | 1,445-1,447
Pre-vaccination |  | 95.9 (94.8, 96.9) | 71.9 (69.5, 74.2)
Post-vaccination |  | 99.6 (99.1, 99.8)b | 98.3 (97.5, 98.9)b
Tdap | 727-728
Pre-vaccination |  | 97.2 (95.8, 98.3) | 74.7 (71.4, 77.8)
Post-vaccination |  | 100 (95.5, 100) | 99.3 (98.4, 99.8)
Anti-diphtheria
BOOSTRIX | 1,440-1,444
Pre-vaccination |  | 85.2 (83.3, 87.0) | 23.7 (21.5, 26.0)
Post-vaccination |  | 98.2 (97.4, 98.8)b | 87.9 (86.1, 89.5)c
Tdap | 720-727
Pre-vaccination |  | 89.2 (86.7, 91.3) | 26.5 (23.3, 29.9)
Post-vaccination |  | 98.6 (97.5, 99.3) | 92.0 (89.8, 93.9)
Tdap = Tetanus Toxoid, Reduced Diphtheria Toxoid and Acellular Pertussis Vaccine, Adsorbed manufactured by Sanofi Pasteur.
ATP = According-to-protocol; CI = Confidence Interval.
a Measured by ELISA.
b Seroprotection rates for BOOSTRIX were non-inferior to the comparator Tdap vaccine (lower limit of 95% CI on the difference of BOOSTRIX minus Tdap ≥-10%).
c Non-inferiority criteria not prospectively defined for this endpoint.

Response to Pertussis Antigens: Booster response rates to the pertussis antigens are shown in Table 13. For the FHA and PRN antigens, the lower limit of the 95% CI for the booster responses exceeded the pre-defined limit of 80% demonstrating an acceptable booster response following BOOSTRIX. The PT antigen booster response lower limit of the 95% CI (74.9%) did not exceed the pre-defined limit of 80%.

Table 13. Booster Responses to the Pertussis Antigens following 1 Dose of BOOSTRIX in Adults Aged 19 to 64 Years (ATP Cohort for Immunogenicity)
Pertussis Antibodies |  | BOOSTRIX
Pertussis Antibodies |  | % Booster Responsea
Pertussis Antibodies | n | (95% CI)
Anti-PT | 1,419 | 77.2 (74.9, 79.3)b
Anti-FHA | 1,433 | 96.9 (95.8, 97.7)c
Anti-PRN | 1,441 | 93.2 (91.8, 94.4)c
ATP = According-to-protocol; CI = Confidence Interval; PT = Pertussis toxin; FHA = Filamentous hemagglutinin; PRN = Pertactin.
a Booster response: In initially seronegative subjects (<5 EL.U./mL), post-vaccination antibody concentrations ≥20 EL.U./mL. In initially seropositive subjects with pre-vaccination antibody concentrations ≥5 EL.U./mL and <20 EL.U./mL, an increase of at least 4 times the pre-vaccination antibody concentration. In initially seropositive subjects with pre-vaccination antibody concentrations ≥20 EL.U./mL, an increase of at least 2 times the pre-vaccination antibody concentration.
b The PT antigen booster response lower limit of the 95% CI did not exceed the pre-defined limit of 80%.
c The FHA and PRN antigens booster response lower limit of the 95% CI exceeded the pre-defined limit of 80%.

The GMCs to each of the pertussis antigens 1 month following a single dose of BOOSTRIX were compared with the GMCs of a subset of infants following a 3-dose primary series of INFANRIX in the German household contact study [see Clinical Studies (14.1)]. Table 14 presents the results for the total immunogenicity cohort in both studies (vaccinated subjects with serology data available for at least 1 pertussis antigen). Anti-PT, anti-FHA, and anti-PRN antibody concentrations observed in adults 1 month after a single dose of BOOSTRIX were non-inferior to those infants following a primary vaccination series with INFANRIX.

Table 14. Ratio of GMCs to Pertussis Antigens following 1 Dose of BOOSTRIX in Adults Aged 19 to 64 Years Compared with 3 Doses of INFANRIX in Infants (Total Immunogenicity Cohort)
Pertussis Antibodies | BOOSTRIX | INFANRIX | GMC Ratio: BOOSTRIX/INFANRIX
Pertussis Antibodies | (n) | (n) | (95% CI)
Anti-PT | 1,460 | 2,884 | 1.39 (1.32, 1.47)a
Anti-FHA | 1,472 | 685 | 7.46 (6.86, 8.12)a
Anti-PRN | 1,473 | 631 | 3.56 (3.10, 4.08)a
GMC = Geometric mean antibody concentration; CI = Confidence Interval; PT = Pertussis toxin; FHA = Filamentous hemagglutinin; PRN = Pertactin.
n = Number of subjects for GMC evaluation.
a BOOSTRIX was non-inferior to INFANRIX (lower limit of 95% CI for the GMC ratio of BOOSTRIX/INFANRIX ≥0.67).

Elderly (Aged 65 Years and Older)

The U.S. elderly (aged 65 years and older) study, a randomized, observer-blinded study (NCT00835237), evaluated the immunogenicity of BOOSTRIX (n = 887) compared with a U.S.-licensed comparator Td vaccine (n = 445) (Sanofi Pasteur). Vaccines were administered as a single dose to subjects who had not received a tetanus-diphtheria booster within 5 years. Among all vaccine recipients, the mean age was approximately 72 years; 54% were female and 95% were White. The immune responses to each of the antigens contained in BOOSTRIX were evaluated in sera obtained approximately 1 month after administration.

Response to Tetanus and Diphtheria Toxoids: Immune responses to tetanus and diphtheria toxoids were measured 1 month after administration of a single dose of BOOSTRIX or a comparator Td vaccine. Anti-tetanus and anti-diphtheria seroprotective rates (≥0.1 IU/mL) were comparable between BOOSTRIX and the comparator Td vaccine (Table 15).

Table 15. Immune Responses to Tetanus and Diphtheria Toxoids following BOOSTRIX or Comparator Td Vaccine in the Elderly Aged 65 Years and Older (ATP Cohort for Immunogenicity)
Anti-Tetanus and Anti-Diphtheria Titers | BOOSTRIX | Td
Anti-Tetanus and Anti-Diphtheria Titers | (n = 844-864) | (n = 430-439)
Anti-tetanus
% ≥0.1 IU/mL (95% CI) | 96.8 (95.4, 97.8)a | 97.5 (95.6, 98.7)
% ≥1.0 IU/mL (95% CI) | 88.8 (86.5, 90.8)a | 90.0 (86.8, 92.6)
Anti-diphtheria
% ≥0.1 IU/mL (95% CI) | 84.9 (82.3, 87.2)a | 86.6 (83.0, 89.6)
% ≥1.0 IU/mL (95% CI) | 52.0 (48.6, 55.4)b | 51.2 (46.3, 56.0)
Td = Tetanus and Diphtheria Toxoids Adsorbed, a U.S.-licensed Td vaccine, manufactured by Sanofi Pasteur.
ATP = According-to-protocol; CI = Confidence Interval.
a Seroprotection rates for BOOSTRIX were non-inferior to the comparator Td vaccine (lower limit of 95% CI on the difference of BOOSTRIX minus Td ≥-10%).
b Non-inferiority criteria not prospectively defined for this endpoint.

Response to Pertussis Antigens: The GMCs to each of the pertussis antigens 1 month following a single dose of BOOSTRIX were compared with the GMCs of a subset of infants following a 3-dose primary series of INFANRIX in the German household contact study [see Clinical Studies (14.1)]. Table 16 presents the results for the total immunogenicity cohort in both studies (vaccinated subjects with serology data available for at least 1 pertussis antigen). Anti-PT, anti-FHA, and anti-PRN antibody concentrations in the elderly 1 month after a single dose of BOOSTRIX were non-inferior to those of infants following a primary vaccination series with INFANRIX.

Table 16. Ratio of GMCs to Pertussis Antigens following 1 Dose of BOOSTRIX in the Elderly Aged 65 Years and Older Compared with 3 Doses of INFANRIX in Infants (Total Immunogenicity Cohort)
Pertussis Antibodies | BOOSTRIX | INFANRIX | GMC Ratio: BOOSTRIX/INFANRIX
Pertussis Antibodies | (n) | (n) | (95% CI)
Anti-PT | 865 | 2,884 | 1.07 (1.00, 1.15)a
Anti-FHA | 847 | 685 | 8.24 (7.45, 9.12)a
Anti-PRN | 878 | 631 | 0.93 (0.79, 1.10)a
GMC = Geometric mean antibody concentration; CI = Confidence Interval; PT = Pertussis toxin; FHA = Filamentous hemagglutinin; PRN = Pertactin.
n = Number of subjects for GMC evaluation.
a BOOSTRIX was non-inferior to INFANRIX (lower limit of 95% CI for the GMC ratio of BOOSTRIX/INFANRIX ≥0.67).

14.3 Study in Pregnant Women

The effectiveness of BOOSTRIX immunization during the third trimester of pregnancy to prevent pertussis among infants younger than 2 months of age was based on a re-analysis within a Bayesian meta-analysis framework of the BOOSTRIX-relevant data from an observational case-control study of Tdap vaccine effectiveness.^4 In this re-analysis, a conditional logistic regression model controlling for age, maternal education, and family size was fit to data from 108 cases (including 4 cases whose mothers received BOOSTRIX during the third trimester) and 183 controls (including 18 whose mothers received BOOSTRIX during the third trimester) matched by age group (<2 weeks old, ≥2 weeks old) and birth hospital. This yielded a preliminary vaccine effectiveness estimate of 78.0% (95% CI: -38.0, 96.5) for vaccination during the third trimester of pregnancy. This preliminary effectiveness estimate was updated using a Bayesian meta-analysis with an informative prior constructed from four observational studies that provided estimates of the vaccine effectiveness of the non-U.S. formulation of BOOSTRIX against pertussis in infants whose mothers were immunized during pregnancy.^(5, 6, 7, 8) To account for potential publication bias, this informative prior was downweighted by combining it with an uninformative prior. When the informative prior has 20% weight, the Bayesian update resulted in estimates of effectiveness of vaccination during the third trimester of pregnancy of 81.5% (95% credible interval:12.9, 94.5). When the informative prior has 90% weight, the Bayesian update resulted in estimates of effectiveness of vaccination during the third trimester of pregnancy of 83.4% (95% credible interval: 55.7, 92.5). The vaccine effectiveness point estimates were consistent, regardless of the weight applied to the informative prior.

14.4 Immune Responses to Vaccination in Infants Born to Mothers Who Received BOOSTRIX During Pregnancy

Data are not available on immune responses to US licensed vaccines administered on the US schedule among infants born to mothers who received BOOSTRIX during pregnancy.

In infants whose mothers received BOOSTRIX (non-US formulation) during the third trimester of pregnancy, antibody responses to a non-US licensed DTaP-containing vaccine were diminished for anti-PT, anti-FHA and anti-PRN following the primary series (NCT 02422264), and for anti-PT and anti-FHA following a booster dose (NCT 02853929) compared to infants who received the same vaccine but whose mothers received placebo during pregnancy. Whether the diminished immune responses observed in vaccinated infants whose mothers received BOOSTRIX (non-US formulation) during pregnancy result in diminished effectiveness of pertussis vaccination in infants is unknown.

14.5 Immunological Evaluation following Revaccination with BOOSTRIX

Adults (Aged 20 to 29 Years)

A multicenter, open-label, controlled study conducted in the United States evaluated the immunogenicity of BOOSTRIX in adults aged 20 to 29 years who received an initial dose of BOOSTRIX (n = 128) or the comparator Td vaccine (MassBiologics) (n = 37) in the U.S. adolescent (aged 10 to 18 years) study (NCT01738477). BOOSTRIX was administered to all subjects 10 years after initial vaccination. The immune responses to each of the antigens contained in BOOSTRIX were evaluated in sera obtained approximately 1 month after vaccine administration. Among all vaccine recipients, the mean age was 23.5 years; 45.5% were female, and 87.9% were White.

Response to Tetanus and Diphtheria Toxoids: The antibody responses to the tetanus and diphtheria toxoids of BOOSTRIX are shown in Table 17. One month after vaccination, anti-tetanus and anti-diphtheria seroprotective rates (≥0.1 IU/mL by ELISA) were comparable between groups.

Table 17. Antibody Responses to Tetanus and Diphtheria Toxoids following BOOSTRIX in Adults Aged 20 to 29 Years (ATP Cohort for Immunogenicity)
 |  | % ≥0.1 IU/mLa | % ≥1.0 IU/mLa
Antibodies | n | (95% CI) | (95% CI)
Anti-tetanus
BOOSTRIXb | 115
Pre-vaccination |  | 100 (96.8, 100) | 74.8 (65.8, 82.4)
Post-vaccination |  | 100 (96.8, 100)c | 100 (96.8, 100)d
Tde | 35
Pre-vaccination |  | 100 (90, 100) | 77.1 (59.9, 89.6)
Post-vaccination |  | 100 (90, 100) | 100 (90, 100)
Anti-diphtheria
BOOSTRIXb | 115
Pre-vaccination |  | 100 (96.8, 100) | 60.9 (51.3, 69.8)
Post-vaccination |  | 100 (96.8, 100)c | 100 (96.8, 100)d
Tde | 35
Pre-vaccination |  | 100 (90, 100) | 65.7 (47.8, 80.9)
Post-vaccination |  | 100 (90,100) | 97.1 (85.1, 99.9)
Td manufactured by MassBiologics.
ATP = According-to-protocol; CI = Confidence Interval.
n = Number of subjects with available results.
a Measured by ELISA.
b Subjects who were revaccinated with BOOSTRIX 10 years after initial vaccination with BOOSTRIX.
c Seroprotection rates following revaccination with BOOSTRIX were non-inferior to an initial dose of BOOSTRIX (Td group) (lower limit of 2-sided 95% CI on the difference for second dose of BOOSTRIX minus first dose of BOOSTRIX ≥-10%).
d Non-inferiority criteria not prospectively defined for this endpoint.
e Subjects who received a dose of BOOSTRIX 10 years after initial vaccination with Td vaccine.

Response to Pertussis Antigens: The GMCs to each of the pertussis antigens 1 month following revaccination with BOOSTRIX in subjects who had received an initial dose of BOOSTRIX 10 years earlier were compared with the GMCs of infants following a 3-dose primary series of PEDIARIX [see Clinical Studies (14.1)]. Table 18 presents the results for the ATP cohort for immunogenicity in both studies. Anti-PT, anti-FHA, and anti-PRN antibody concentrations observed in adults 1 month after revaccination with BOOSTRIX were non-inferior to those of infants following a primary vaccination series with PEDIARIX.

Table 18. Ratio of GMCs to Pertussis Antigens following BOOSTRIX in Adults Aged 20 to 29 Years Compared with 3 Doses of PEDIARIX in Infants (ATP Cohort for Immunogenicity)
 | BOOSTRIXa | PEDIARIX | GMC Ratio: BOOSTRIX/PEDIARIX
Pertussis Antibodies | (n) | (n) | (95% CI)
Anti-PT | 115 | 149 | 1.81 (1.48, 2.21)b
Anti-FHA | 115 | 149 | 2.37 (1.98, 2.83)b
Anti-PRN | 115 | 149 | 9.87 (7.80, 12.49)b
GMC = Geometric mean antibody concentration; CI = Confidence Interval; PT = Pertussis toxin; FHA = Filamentous hemagglutinin; PRN = Pertactin.
n = Number of subjects for GMC evaluation.
a Subjects who were revaccinated with BOOSTRIX 10 years after initial vaccination with BOOSTRIX.
b BOOSTRIX was non-inferior to PEDIARIX (lower limit of 95% CI for the GMC ratio of BOOSTRIX/PEDIARIX ≥0.67).

Adults (Aged 28 to 73 Years)

A multicenter, open-label, controlled study conducted in the United States evaluated the immunogenicity of BOOSTRIX in adults aged 28 to 73 years who received an initial dose of BOOSTRIX (n = 309) or the licensed comparator Tdap vaccine (Sanofi Pasteur) (n = 138) in the U.S. adult (aged 19 to 64 years) study (NCT00489970). BOOSTRIX was administered to all subjects 9 years after initial vaccination. A control group of newly enrolled adult subjects received an initial dose of BOOSTRIX (n = 362). The immune responses to each of the antigens contained in BOOSTRIX were evaluated in sera obtained approximately 1 month after vaccine administration. Of the subjects enrolled in this study, the mean age was 52.1 years; 62.6% were female, and 86.6% were White.

Response to Tetanus and Diphtheria Toxoids: The antibody responses to the tetanus and diphtheria toxoids of BOOSTRIX are shown in Table 19. One month after vaccination, anti-tetanus and anti-diphtheria seroprotective rates (≥0.1 IU/mL by ELISA) were comparable between groups.

Table 19. Antibody Responses to Tetanus and Diphtheria Toxoids following BOOSTRIX in Adults Aged 28 to 73 Years (ATP Cohort for Immunogenicity)
Antibodies | n | % ≥0.1 IU/mLa; (95% CI) | % ≥1.0 IU/mLa; (95% CI) | % Booster Responseb; (95% CI)
Anti-tetanus
BOOSTRIXc | 268-271
Pre-vaccination |  | 98.1 (95.7, 99.4) | 78.7 (73.3, 83.5)
Post-vaccination |  | 100 (98.6, 100)d | 99.3 (97.4, 99.9)e | 47.0 (40.9, 53.2)f
Tdapg | 120-121
Pre-vaccination |  | 100 (97.0, 100) | 84.2 (76.4, 90.2)
Post-vaccination |  | 100 (97.0, 100)d | 100 (97.0, 100)e | 36.7 (28.1, 45.9)f
Controlh | 324-327
Pre-vaccination |  | 93.8 (90.6, 96.2) | 71.3 (66.0, 76.2)
Post-vaccination |  | 99.7 (98.3, 100) | 97.6 (95.2, 98.9) | 48.5 (42.9, 54.0)
Anti-diphtheria
BOOSTRIXc | 269-271
Pre-vaccination |  | 91.1 (87.0, 94.2) | 42.4 (36.4, 48.5)
Post-vaccination |  | 99.3 (97.4, 99.9)d | 91.9 (88.0, 94.8)e | 62.8 (56.7, 68.6)f
Tdapg | 118-121
Pre-vaccination |  | 95.8 (90.4, 98.6) | 45.8 (36.6, 55.2)
Post-vaccination |  | 99.2 (95.5, 100)d | 93.4 (87.4, 97.1)e | 60.2 (50.7, 69.1)f
Controlh | 324-326
Pre-vaccination |  | 81.8 (77.1, 85.8) | 28.4 (23.5, 33.6)
Post-vaccination |  | 97.9 (95.6, 99.1) | 86.5 (82.3, 90.0) | 68.7 (63.4, 73.7)
Tdap = Tetanus Toxoid, Reduced Diphtheria Toxoid and Acellular Pertussis Vaccine, Adsorbed manufactured by Sanofi Pasteur.
ATP = According-to-protocol; CI = Confidence Interval.
n = Number of subjects with available results.
a Measured by ELISA.
b Booster response: In subjects with pre-vaccination <0.1 IU/mL, post-vaccination concentration ≥0.4 IU/mL. In subjects with pre-vaccination concentration ≥0.1 IU/mL, an increase of at least 4 times the pre-vaccination concentration.
c Subjects who were revaccinated with BOOSTRIX 9 years after initial vaccination with BOOSTRIX.
d Seroprotection rates following a dose of BOOSTRIX in subjects who had received an initial dose of BOOSTRIX or the licensed comparator Tdap vaccine were non-inferior to an initial dose of BOOSTRIX (Control Group) (lower limit of 97.5% CI on the difference of BOOSTRIX minus Control Group ≥-10%).
e Non-inferiority criteria not prospectively defined for this endpoint.
f The booster response rates following a dose of BOOSTRIX in subjects who had received an initial dose of BOOSTRIX or the licensed comparator Tdap vaccine did not meet the pre-defined non-inferiority criteria (lower limit of the 97.5% CIs ≥-10% [BOOSTRIX minus Control Group] and [Tdap minus Control Group]).
g Subjects who received a dose of BOOSTRIX 9 years after initial vaccination with Tdap vaccine.
h Control Group = Newly enrolled subjects who received an initial dose of BOOSTRIX.

Response to Pertussis Antigens: The GMCs to each of the pertussis antigens 1 month following a dose of BOOSTRIX in subjects who had received an initial dose of BOOSTRIX or the licensed comparator Tdap vaccine (Sanofi Pasteur) 9 years earlier were compared with the GMCs of infants following a 3-dose primary series of PEDIARIX [see Clinical Studies (14.1)]. Table 20 presents the results for the ATP cohort for immunogenicity in both studies. Anti-PT, anti-FHA, and anti-PRN antibody concentrations observed in adults 1 month after a dose of BOOSTRIX were non-inferior to those of infants following a primary vaccination series with PEDIARIX.

Table 20. Ratio of GMCs to Pertussis Antigens following BOOSTRIX in Adults Aged 28 to 73 Years Compared with 3 Doses of PEDIARIX in Infants (ATP Cohort for Immunogenicity)
Pertussis Antibodies | Vaccinated with BOOSTRIX 9 Years after Initial Vaccination with: |  | PEDIARIX; (n) | GMC Ratio:
Pertussis Antibodies | BOOSTRIX; (n) | Tdap; (n) | PEDIARIX; (n) | BOOSTRIX/; PEDIARIX; (97.5% CI) | Tdap/; PEDIARIX; (97.5% CI)
Anti-PT | 271 | 121 | 149 | 1.33; (1.09, 1.61)a | 1.46; (1.14, 1.87)a
Anti-FHA | 271 | 121 | 149 | 2.02; (1.72, 2.37)a | 2.07; (1.68, 2.57)a
Anti-PRN | 271 | 121 | 149 | 8.64; (6.85, 10.89)a | 10.90; (8.27, 14.38)a
Tdap = Tetanus Toxoid, Reduced Diphtheria Toxoid and Acellular Pertussis Vaccine, Adsorbed manufactured by Sanofi Pasteur.
GMC = Geometric mean antibody concentration; CI = Confidence Interval; PT = Pertussis toxin; FHA = Filamentous hemagglutinin; PRN = Pertactin.
n = Number of subjects for GMC evaluation.
a BOOSTRIX was non-inferior to PEDIARIX (lower limit of 97.5% CI for the GMC ratio of BOOSTRIX/PEDIARIX ≥0.67).

Compared with the Control Group, non-inferiority of booster response rates to the pertussis antigens following a dose of BOOSTRIX in subjects who had received an initial dose of BOOSTRIX or another licensed Tdap vaccine (Sanofi Pasteur) was achieved for the PT antigen [BOOSTRIX minus Control Group] and the FHA antigen [Tdap minus Control Group], respectively (Table 21). Non-inferiority was not achieved for FHA and PRN booster response rates [BOOSTRIX minus Control Group] or for PT and PRN booster response rates [Tdap minus Control Group].

Table 21. Booster Responses to the Pertussis Antigens following BOOSTRIX in Adults Aged 28 to 73 Years (ATP Cohort for Immunogenicity)
Pertussis Antibodies | n | % Booster Responsea; (95% CI) | Difference in Booster Response Rates
Pertussis Antibodies | n | % Booster Responsea; (95% CI) | BOOSTRIX minus; Control Group; (97.5% CI) | Tdap minus Control Group (97.5% CI)
Anti-PT
BOOSTRIXb | 271 | 86.7 (82.1, 90.5) | -2.85 (-9.09, 3.08)c
Tdapd | 120 | 88.3 (81.2, 93.5) |  | -1.24 (-10.03, 5.57)
Controle | 326 | 89.6 (85.7, 92.7)
Anti-FHA
BOOSTRIXb | 271 | 85.6 (80.9, 89.6) | -7.05 (-13.16, -1.40)
Tdapd | 120 | 96.7 (91.7, 99.1) |  | 4.01 (-2.38, 8.66)c
Controle | 327 | 92.7 (89.3, 95.2)
Anti-PRN
BOOSTRIXb | 271 | 77.5 (72.0, 82.3) | -10.32 (-17.50, -3.38)
Tdapd | 118 | 83.1 (75.0, 89.3) |  | -4.76 (-14.53, 3.18)
Controle | 320 | 87.8 (83.7, 91.2)
Tdap = Tetanus Toxoid, Reduced Diphtheria Toxoid and Acellular Pertussis Vaccine, Adsorbed manufactured by Sanofi Pasteur.
ATP = According-to-protocol; CI = Confidence Interval; PT = Pertussis toxin; FHA = Filamentous hemagglutinin; PRN = Pertactin.
n = Number of subjects with available results.
a Booster response: In initially seronegative subjects (pre-vaccination antibody concentration below the assay cut-off), post-vaccination antibody concentrations ≥4 times the assay cut-off. In initially seropositive subjects with pre-vaccination antibody concentrations <4 times the assay cut-off, an increase of at least 4 times the pre-vaccination antibody concentration. In initially seropositive subjects with pre-vaccination antibody concentrations ≥4 times the assay cut-off, an increase of at least 2 times the pre-vaccination antibody concentration. Assay cut-offs: anti-PT = 2.693 IU/mL; anti-FHA = 2.046 IU/mL; anti-PRN = 2.187 IU/mL.
b Subjects who were revaccinated with BOOSTRIX 9 years after initial vaccination with BOOSTRIX.
c Non-inferiority of the booster response rate for each pertussis antigen was demonstrated if the lower limit of the 97.5% CI [BOOSTRIX minus Control Group] or [Tdap minus Control Group] was above the pre-defined limit of -10%.
d Subjects who received a dose of BOOSTRIX 9 years after initial vaccination with Tdap vaccine.
e Control Group = Newly enrolled subjects who received an initial dose of BOOSTRIX.

14.6 Concomitant Administration with Meningococcal Conjugate Vaccine

The concomitant use of BOOSTRIX and a tetravalent meningococcal (groups A, C, Y, and W-135) conjugate vaccine (Sanofi Pasteur) was evaluated in a randomized study in healthy adolescents aged 11 to 18 years (NCT00282295). A total of 1,341 adolescents were vaccinated with BOOSTRIX. Of these, 446 subjects received BOOSTRIX administered concomitantly with meningococcal conjugate vaccine at different injection sites, 446 subjects received BOOSTRIX followed by meningococcal conjugate vaccine 1 month later, and 449 subjects received meningococcal conjugate vaccine followed by BOOSTRIX 1 month later.

Immune responses to diphtheria and tetanus toxoids (% of subjects with anti-tetanus and anti-diphtheria antibodies ≥1.0 IU/mL by ELISA), pertussis antigens (booster responses and GMCs), and meningococcal antigens (vaccine responses) were measured 1 month (range: 30 to 48 days) after concomitant or separate administration of BOOSTRIX and meningococcal conjugate vaccine. For BOOSTRIX given concomitantly with meningococcal conjugate vaccine compared with BOOSTRIX administered first, non-inferiority was demonstrated for all antigens, with the exception of the anti-PRN GMC. The lower limit of the 95% CI for the GMC ratio was 0.54 for anti-PRN (pre-specified limit ≥0.67). For the anti-PRN booster response, non-inferiority was demonstrated. It is not known if the efficacy of BOOSTRIX is affected by the reduced response to PRN.

There was no evidence that BOOSTRIX interfered with the antibody responses to the meningococcal antigens when measured by rabbit serum bactericidal assays (rSBA) when given concomitantly or sequentially (meningococcal conjugate vaccine followed by BOOSTRIX or BOOSTRIX followed by meningococcal conjugate vaccine).

14.7 Concomitant Administration with FLUARIX (Inactivated Influenza Vaccine)

The concomitant use of BOOSTRIX and FLUARIX was evaluated in a multicenter, open-label, randomized, controlled study (NCT00385255) of 1,497 adults aged 19 to 64 years. In one group, subjects received BOOSTRIX and FLUARIX concurrently (n = 748). The other group received FLUARIX at the first visit, then 1 month later received BOOSTRIX (n = 749). Sera was obtained prior to and 1 month following concomitant or separate administration of BOOSTRIX and/or FLUARIX, as well as 1 month after the separate administration of FLUARIX.

Immune responses following concurrent administration of BOOSTRIX and FLUARIX were non-inferior to separate administration for diphtheria (seroprotection defined as ≥0.1 IU/mL), tetanus (seroprotection defined as ≥0.1 IU/mL and based on concentrations ≥1.0 IU/mL), PT antigen (anti-PT GMC), and influenza antigens (percent of subjects with hemagglutination-inhibition [HI] antibody titer ≥1:40 and ≥4-fold rise in HI titer). Non-inferiority criteria were not met for the anti-pertussis antigens FHA and PRN. The lower limit of the 95% CI of the GMC ratio was 0.64 for anti-FHA and 0.60 for anti-PRN and the pre-specified limit was ≥0.67. It is not known if the efficacy of BOOSTRIX is affected by the reduced response to FHA and PRN.

14.8 Concomitant Administration with SHINGRIX (Zoster Vaccine Recombinant, Adjuvanted)

The concomitant use of BOOSTRIX and SHINGRIX was evaluated in an open-label clinical study (NCT 02052596) of subjects aged 50 years and older. Subjects in Group 1 received BOOSTRIX and the first dose of SHINGRIX at Month 0 and the second dose of SHINGRIX at Month 2 (n = 412; concomitant administration group). Subjects in Group 2 received BOOSTRIX at Month 0, the first dose of SHINGRIX at Month 2, and the second dose of SHINGRIX at Month 4 (n = 418; separate administration control group). The mean age of the subjects was 63 years; 54% were female. The majority of subjects were White (87%), followed by Black (11%), and other racial groups; 2% were of American Hispanic or Latino ethnicity.

The immune responses to BOOSTRIX (anti-D, anti-T, and antibodies to pertussis antigens) were measured 1 month after administration of the single dose of BOOSTRIX. The immune response to SHINGRIX was measured by anti-gE Ab concentrations 1 month after the second dose of SHINGRIX. Concomitant administration showed no evidence for interference in the immune response to the antigen contained in SHINGRIX or the antigens contained in BOOSTRIX, with the exception of one of the pertussis antigens (pertactin), which did not satisfy the noninferiority criterion: the UL of the 95% CI for the adjusted GMC ratio (separate administration control group/concomitant administration group) for anti-pertactin antibody was 1.58 (noninferiority criterion <1.5). The clinical significance of the reduced immune response to pertactin is unknown.

15 REFERENCES

1. Institute of Medicine (IOM). Stratton KR, Howe CJ, Johnston RB, eds. Adverse events associated with childhood vaccines. Evidence bearing on causality. Washington, DC: National Academy Press; 1994.
2. Wassilak SGF, Roper MH, Kretsinger K, and Orenstein WA. Tetanus Toxoid. In: Plotkin SA, Orenstein WA, and Offit PA, eds. Vaccines. 5th ed. Saunders; 2008:805-839.
3. Vitek CR and Wharton M. Diphtheria Toxoid. In: Plotkin SA, Orenstein WA, and Offit PA, eds. Vaccines. 5th ed. Saunders; 2008:139-156.
4. Skoff TH, Blain AE, Watt J, et al. Impact of the US maternal tetanus, diphtheria, and acellular pertussis vaccination program on preventing pertussis in infants <2 months of age: a case-control evaluation. Clin Infect Dis. 2017; 65 (12): 1977-83.
5. Bellido-Blasco J, Guiral-Rodrigo S, Míguez-Santiyán A, Salazar-Cifre A, González-Morán F. A case-control study to assess the effectiveness of pertussis vaccination during pregnancy on newborns, Valencian community, Spain, 1 March 2015 to 29 February 2016. Euro Surveill. 2017;22(22).
6. Saul N, Wang K, Bag S, Baldwin H, Alexander K, Chandra M, et al. Effectiveness of maternal pertussis vaccination in preventing infection and disease in infants: The NSW Public Health Network case-control study. Vaccine. 2018;36(14):1887-1892.
7. Uriarte PS, Rodríguez SSJ, Sancristobal IG, Agirre NM. Effectiveness of dTpa vaccination during pregnancy in preventing whooping cough in infants under 3 months of age. Bizkaia, Basque Country, Spain. Heliyon. 2019;5(2):e01207.
8. Andrews A, Campbell H, Riberio S, Fry N, Amirthalingham G. Boostrix-IPV Report: Effectiveness of Maternal Pertussis Vaccination in Prevention of Confirmed Pertussis in Children in England Using the Screening Method Report to 30 September 2018. Public Health England. Unpublished. 2020.

16 HOW SUPPLIED/STORAGE AND HANDLING

Product: 50090-1377

NDC: 50090-1377-0 .5 mL in a SYRINGE / 10 in a CARTON

17 PATIENT COUNSELING INFORMATION

Provide the following information to the vaccine recipient, parent, or guardian:

- Inform of the potential benefits and risks of immunization with BOOSTRIX.
- Inform about the potential for adverse reactions that have been temporally associated with administration of BOOSTRIX or other vaccines containing similar components.
- Instruct vaccine recipient to report any adverse events to their healthcare provider.
- Advise women who receive BOOSTRIX during pregnancy to enroll in the pregnancy registry [see Use in Specific Populations (8.1)].
- Give the Vaccine Information Statements, which are required by the National Childhood Vaccine Injury Act of 1986 prior to immunization. These materials are available free of charge at the Centers for Disease Control and Prevention (CDC) website (www.cdc.gov/vaccines).

BOOSTRIX, FLUARIX, INFANRIX, PEDIARIX, SHINGRIX, and TIP‑LOK are trademarks owned by or licensed to the GSK group of companies. The other brands listed are trademarks owned by or licensed to their respective owners and are not owned by or licensed to the GSK group of companies. The makers of these brands are not affiliated with and do not endorse the GSK group of companies or its products.
Manufactured by GlaxoSmithKline Biologicals

Rixensart, Belgium, U.S. License 1617, and

GSK Vaccines GmbH

Marburg, Germany, U.S. License 1617

Distributed by GlaxoSmithKline

Durham, NC 27701

©2024 GSK group of companies or its licensor.

BTX:38PI